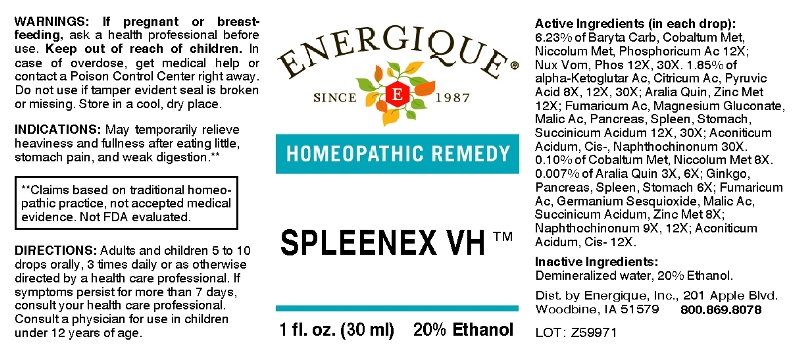 DRUG LABEL: Spleenex
NDC: 44911-0294 | Form: LIQUID
Manufacturer: Energique, Inc.
Category: homeopathic | Type: HUMAN OTC DRUG LABEL
Date: 20241030

ACTIVE INGREDIENTS: AMERICAN GINSENG 3 [hp_X]/1 mL; GINKGO 6 [hp_X]/1 mL; SUS SCROFA PANCREAS 6 [hp_X]/1 mL; SUS SCROFA SPLEEN 6 [hp_X]/1 mL; SUS SCROFA STOMACH 6 [hp_X]/1 mL; GERMANIUM SESQUIOXIDE 8 [hp_X]/1 mL; COBALT 8 [hp_X]/1 mL; NICKEL 8 [hp_X]/1 mL; ZINC 8 [hp_X]/1 mL; OXOGLURIC ACID 8 [hp_X]/1 mL; ANHYDROUS CITRIC ACID 8 [hp_X]/1 mL; FUMARIC ACID 8 [hp_X]/1 mL; MALIC ACID 8 [hp_X]/1 mL; PYRUVIC ACID 8 [hp_X]/1 mL; SUCCINIC ACID 8 [hp_X]/1 mL; NAPHTHOQUINE 9 [hp_X]/1 mL; BARIUM CARBONATE 12 [hp_X]/1 mL; PHOSPHORIC ACID 12 [hp_X]/1 mL; ACONITIC ACID, (Z)- 12 [hp_X]/1 mL; MAGNESIUM GLUCONATE 12 [hp_X]/1 mL; STRYCHNOS NUX-VOMICA SEED 12 [hp_X]/1 mL; PHOSPHORUS 12 [hp_X]/1 mL
INACTIVE INGREDIENTS: WATER; ALCOHOL

DRUG FACTS:

ACTIVE INGREDIENTS:

(in each drop): 6.23% Baryta Carbonica 12X, Cobaltum Metallicum 12X, Niccolum Metallicum 12X, Phosphoricum Acidum 12X; Nux Vomica 12X, 30x, Phosphorus 12X, 30X. 1.85% of alpha-Ketoglutaricum Acidum 8X, 12X, 30X, Citricum Acidum 8X, 12X, 30X, Pyruvic Acid 8X, 12X, 30X; Aralia Quinquefolia 12X, Zincum Metallicum 12X; Fumaricum Acidum 12X, 30X, Magnesium Gluconicum Dihydricum 12X, 30X, Malic Acid 12X, 30X, Pancreas Suis 12X, 30X, Spleen (Suis) 12X, 30X, Stomach (Suis) 12X, 30X, Succinicum Acidum 12X, 30X; Aconiticum Acidum, Cis 30X, Naphthochinonum 30X. 0.10% of Cobaltum Metallicum 8X, Niccolum Metallicum 8X. 0.007% of Aralia Quinquefolia 3X, 6X; Ginkgo Biloba 6X, Pancreas Suis 6X, Spleen (Suis) 6X, Stomach (Suis) 6X; Fumaricum Acidum 8X, Germanium Sesquioxide 8X, Malic Acid 8X, Succinicum Acidum 8X, Zincum Metallicum 8X; Naphthochinonum 9X, 12X; Aconiticum Acidum, Cis 12X.

INDICATIONS:

May temporarily relieve heaviness and fullness after eating little, stomach pain, and weak digestion.**

**Claims based on traditional homeopathic practice, not accepted medical evidence. Not FDA evaluated.

WARNINGS:

If pregnant or breast-feeding, ask a health professional before use.
Keep out of reach of children. In case of overdose, get medical help or contact a Poison Control Center right away.
Do not use if tamper evident seal is broken or missing. Store in a cool, dry place.

Keep out of reach of children. In case of overdose, get medical help or contact a Poison Control Center right away.

DIRECTIONS:

Adults and children 5 to 10 drops orally, 3 times daily or as otherwise directed by a health care professional. If symptoms persist for more than 7 days, consult your health care professional. Consult a physician for use in children under 12 years of age.

INDICATIONS:

May temporarily relieve heaviness and fullness after eating little, stomach pain, weak digestion.**

**Claims based on traditional homeopathic practice, not accepted medical evidence. Not FDA evaluated.

INACTIVE INGREDIENTS:

Demineralized water, 20% Ethanol.

QUESTIONS:

Dist. by Energique, Inc.
201 Apple Blvd
Woodbine, IA 51579 800.869.8078

PACKAGE LABEL DISPLAY:

ENERGIQUE

SINDE 1987

HOMEOPATHIC REMEDY

SPLEENEX VH

1 fl. oz. (30 ml)